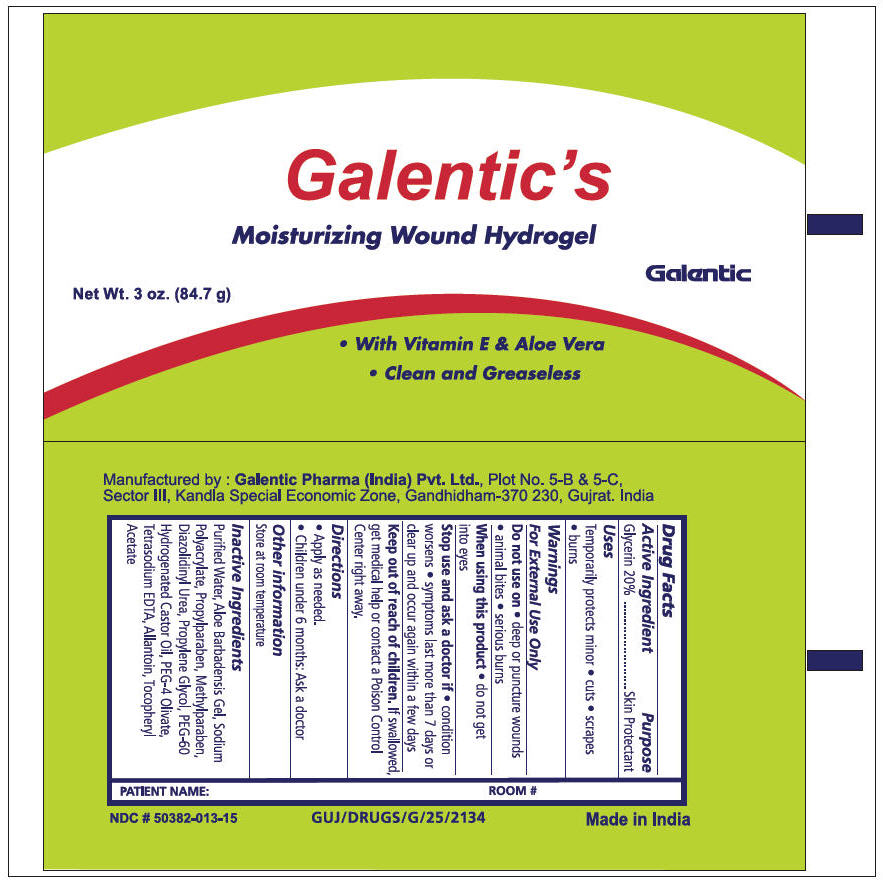 DRUG LABEL: Galentic Hydrogel
NDC: 50382-013 | Form: GEL
Manufacturer: Galentic Pharma (India) Private Limited
Category: otc | Type: HUMAN OTC DRUG LABEL
Date: 20180619

ACTIVE INGREDIENTS: GLYCERIN 20 g/100 g
INACTIVE INGREDIENTS: ALLANTOIN; ALOE VERA LEAF; DIAZOLIDINYL UREA; METHYLPARABEN; PROPYLENE GLYCOL; PEG-60 HYDROGENATED CASTOR OIL; PROPYLPARABEN; WATER; EDETATE SODIUM; .ALPHA.-TOCOPHEROL ACETATE

Galentic's Moisturizing Wound Hydrogel

Active Ingredient

Glycerin 20.0%

Purpose

Skin Protectant

• USES

Temporarily protects minor

- Cuts
- Scrapes
- Burns

• WARNINGS

For external use only

• DO NOT USE ON

- Deep or puncture wounds
- Animal bites
- Serious burns

• WHEN USING THIS PRODUCT

Do not get into eyes

• STOP USE AND ASK A DOCTOR IF

- Condition worsens
- Symptoms last more than 7 days or clear up and occur again a few days

• KEEP OUT OF REACH OF CHILDREN

If swallowed, get medical help or contact a Poison Control Center right away.

• DIRECTIONS

- Apply as needed.
- Children under 6 months: Ask a doctor

• OTHER INFORMATION

Store at room temperature

• INACTIVE INGREDIENT

Allantoin, Aloe Barbadensis gel, Diazolidinyl urea, Methylparaben, PEG-4 Olivate, PEG-60 Hydrogenated castor oil, Propylene glycol, Propylparaben, Purified water, Sodium polyacrylate, Tetrasodium EDTA, Tocopheryl acetate

Manufactured by : Galentic Pharma (India) Pvt. Ltd., Plot No. 5-B & 5-C,
Sector III, Kandla Special Economic Zone, Gandhidham-370 230, Gujrat. India

PRINCIPAL DISPLAY PANEL - 84.7 g Tube Label

Galentic's
Moisturizing Wound Hydrogel

Galentic

Net Wt. 3 oz. (84.7 g)

- With Vitamin E & Aloe Vera
- Clean and Greaseless